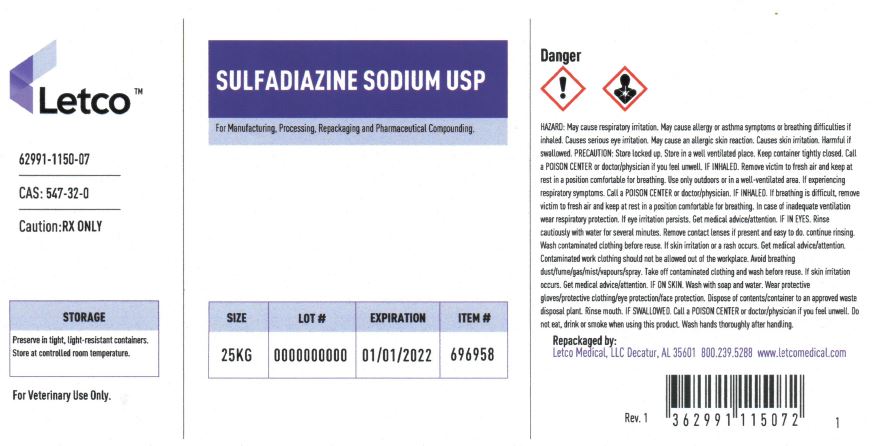 DRUG LABEL: Sulfadiazine sodium
NDC: 62991-1150 | Form: POWDER
Manufacturer: LETCO MEDICAL, LLC
Category: other | Type: BULK INGREDIENT - ANIMAL DRUG
Date: 20240718

ACTIVE INGREDIENTS: SULFADIAZINE SODIUM 1 g/1 g

Sulfadiazine sodium

PACKAGE LABEL

Sulfadiazine Sodium USP 25kg